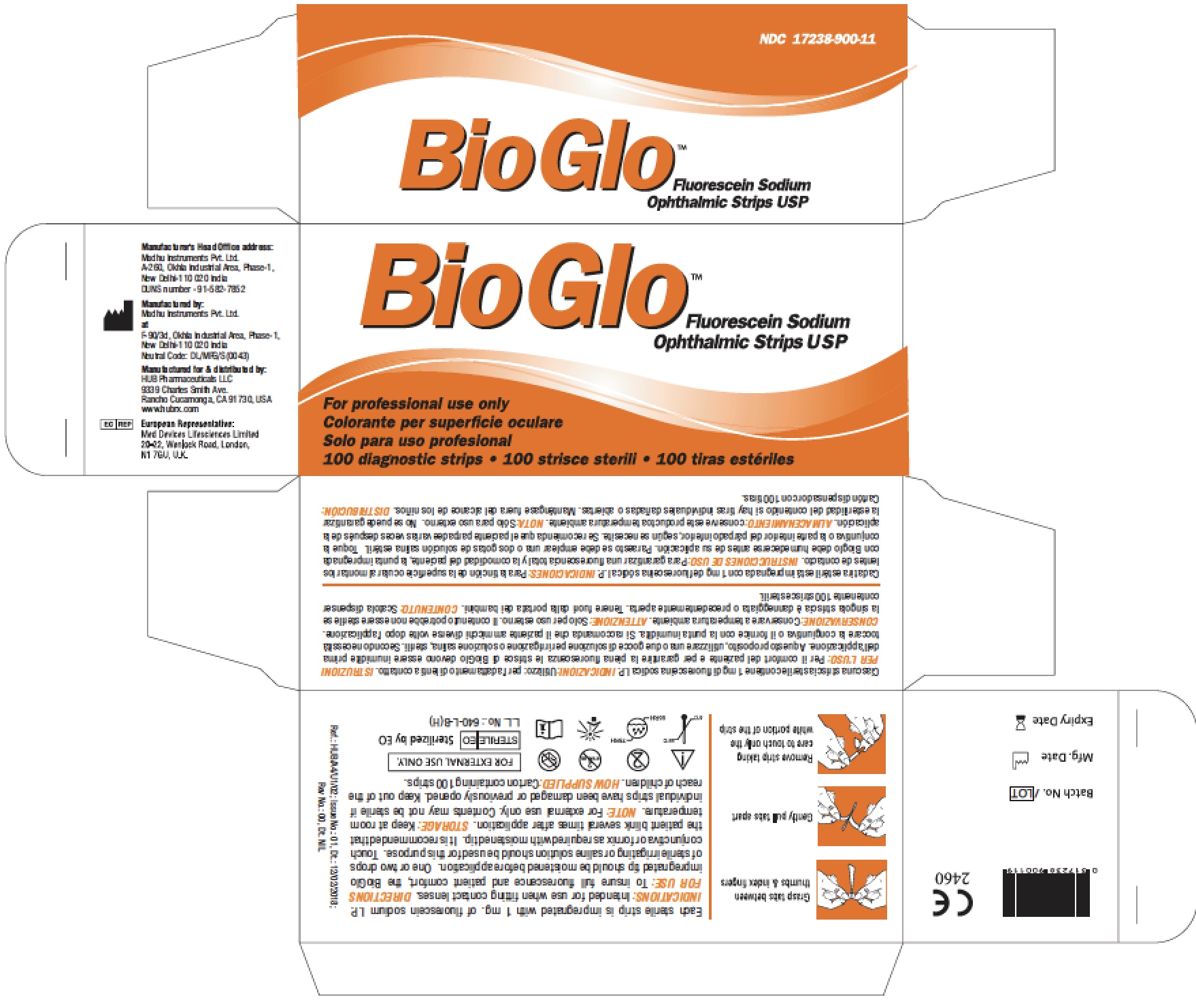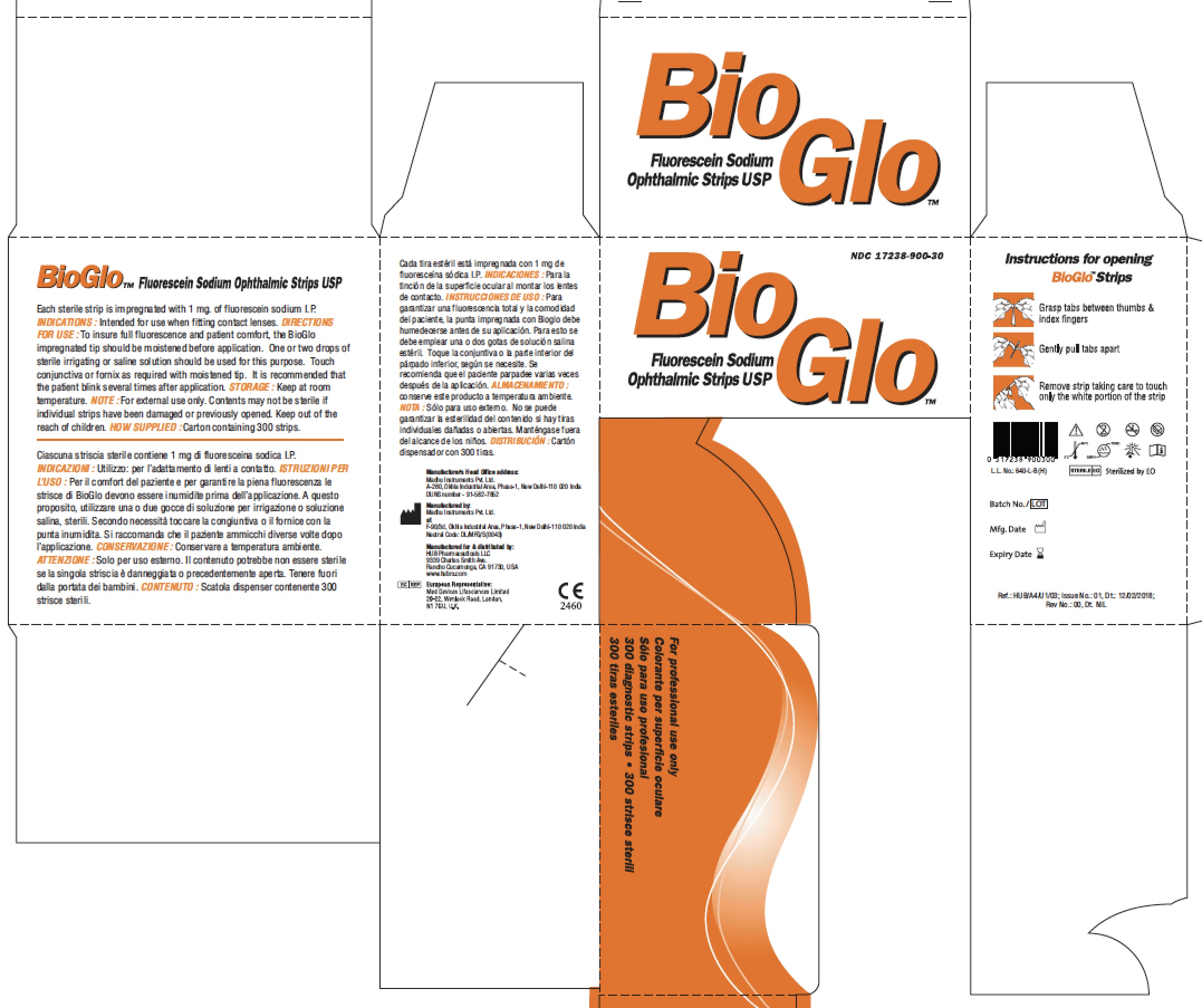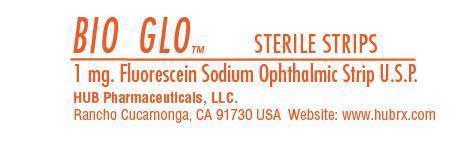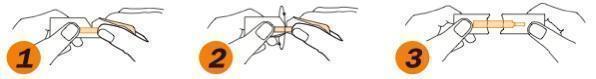 DRUG LABEL: BioGlo
NDC: 17238-900 | Form: STRIP
Manufacturer: HUB Pharmaceuticals, Inc.
Category: prescription | Type: HUMAN PRESCRIPTION DRUG LABEL
Date: 20240101

ACTIVE INGREDIENTS: FLUORESCEIN SODIUM 1 mg/1 mg

BIO GLO (fluorescein sodium) strip

Product Facts

Each sterile strip is impregnated with 1 mg. of fluorescein sodium U.S.P.

INDICATIONS:

For staining the anterior segment of the eye when fitting contact lenses, in disclosing corneal injury and in applanation tonometry.

DIRECTIONS FOR USE:

To insure full fluorescence and patient comfort, the BioGlo impregnated tip should be moistened before application. One or two drops of sterile irrigating or saline solution should be used for this purpose. Touch conjunctiva or fornix as required with moistened tip. It is recommended that the patient blink several times after application.

1. Grasp tabs between thumbs & index fingers
2. Gently pull tabs apart
3. Remove strip taking care to touch only the white portion of the strip

STORAGE:

Keep at room temperature.

NOTE:

For external use only. Contents may not be sterile if individual strips have been damaged or previously opened.

Keep out of reach of children

HOW SUPPLIED:

Dispenser carton containing 100 or 300 strips.

HUB Pharmaceuticals, LLC

Rancho Cucamonga, CA 91730

www.hubrx.com

Mfr. Lic. No. G/1197

European Representative:

Biovision Limited

Wayside, Tring Road, Wellhead, Dunstable, BEDS LU6 2JU, UK

Representative Packaging:

17238-900-99: BioGlo Individual Pouch (above)

17238-900-11: Dispenser Carton containing 100 strips (above)

17238-900-30: Dispenser Carton containing 300 strips (above)